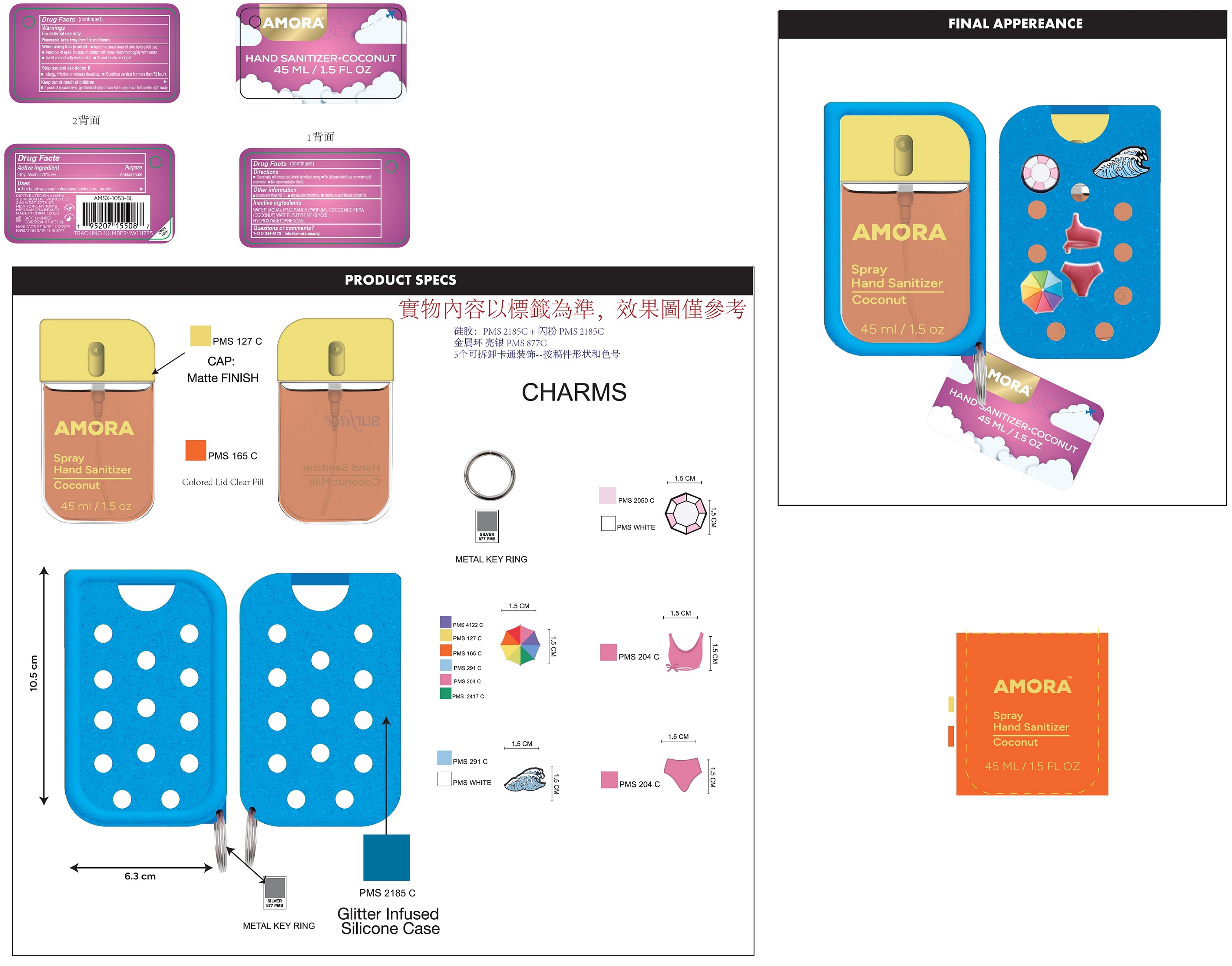 DRUG LABEL: Amora Hand Sanitizer Coconut
NDC: 85179-038 | Form: SPRAY
Manufacturer: I World LLC
Category: otc | Type: HUMAN OTC DRUG LABEL
Date: 20260127

ACTIVE INGREDIENTS: ALCOHOL 70 mL/100 mL
INACTIVE INGREDIENTS: COCOS NUCIFERA WHOLE; WATER; COCONUT WATER; BUTYLENE GLYCOL; HYDROXYACETOPHENONE

Amora Spray Hand Sanitizer Coconut

Active ingredient

Ethyl Alcohol 70% v/v

Purpose

Antibacterial

Uses

- For hand-washing to decrease bacteria on the skin.

Warnings

For external use only.

Flammabel, keep away from fire and flames

when using this product

- test on a small area of skin before full use.
- keep out of eyes. In case of contact with eyes, flush throughly with water.
- Avoid contact with broken skin.
- Do not inhale or ingest.

Stop use and ask doctor if

- allergy, irritation or redness develops.
- Condition persists for more than 72 hours.

Keep out of reach of children.

- If product is swallowed, get medical help or contact a poison control centre right away.

Directions

- Spray hands with product and allow to dry without wiping.
- For children under 6, use only under adult supervision.
- Not recommended for infants.

Other information

- Do not store above 105° F
- May discolor some fabrics
- Harmful to wood finishes and plastics

Inactive ingredients

WATER (AQUA), FRAGRANCE (PARFUM), COCOS NUCIFERA COCONUT WATER, BUTYLENE GLYCOL, HYDROXYACETOPHENONE.

Questions or comments?

1-212-244-5170 info@amora.beauty